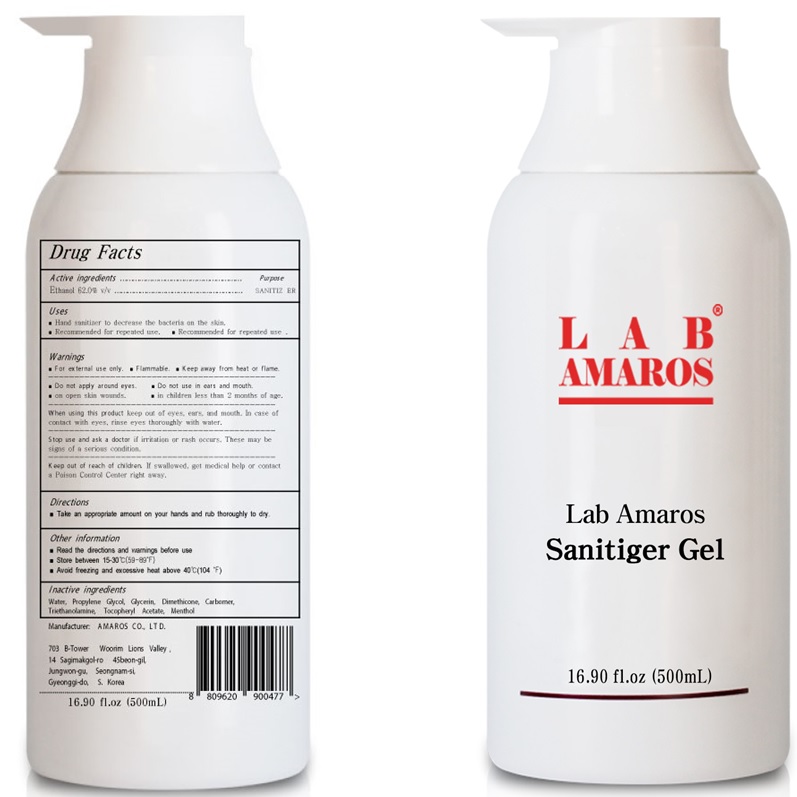 DRUG LABEL: Lab Amaros Camellia Sanitizer
NDC: 60899-120 | Form: GEL
Manufacturer: AMAROS CO., LTD.
Category: otc | Type: HUMAN OTC DRUG LABEL
Date: 20210528

ACTIVE INGREDIENTS: ALCOHOL 310 mL/500 mL
INACTIVE INGREDIENTS: Water; Propylene Glycol; Glycerin; Dimethicone; CARBOMER HOMOPOLYMER, UNSPECIFIED TYPE; TROLAMINE; .ALPHA.-TOCOPHEROL ACETATE; Menthol

ACTIVE INGREDIENT

Ethanol 62.0% v/v

INACTIVE INGREDIENTS

Water, Propylene Glycol, Glycerin, Dimethicone, Carbomer, Triethanolamine, Tocopheryl Acetate, Menthol

PURPOSE

SANITIZER

WARNINGS

For external use only. Flammable. Keep away from heat or flame
--------------------------------------------------------------------------------------------------------
Do not use
• in children less than 2 months of age
• on open skin wounds
--------------------------------------------------------------------------------------------------------
When using this product keep out of eyes, ears, and mouth. In case of contact with eyes, rinse eyes thoroughly with water.
--------------------------------------------------------------------------------------------------------
Stop use and ask a doctor if irritation or rash occurs. These may be signs of a serious condition.

Keep out of reach of children. If swallowed, get medical help or contact a Poison Control Center right away.

Uses

■ Hand sanitizer to decrease the bacteria on the skin.
■ Recommended for repeated use.

Directions

■ Take an appropriate amount on your hands and rub thoroughly to dry.